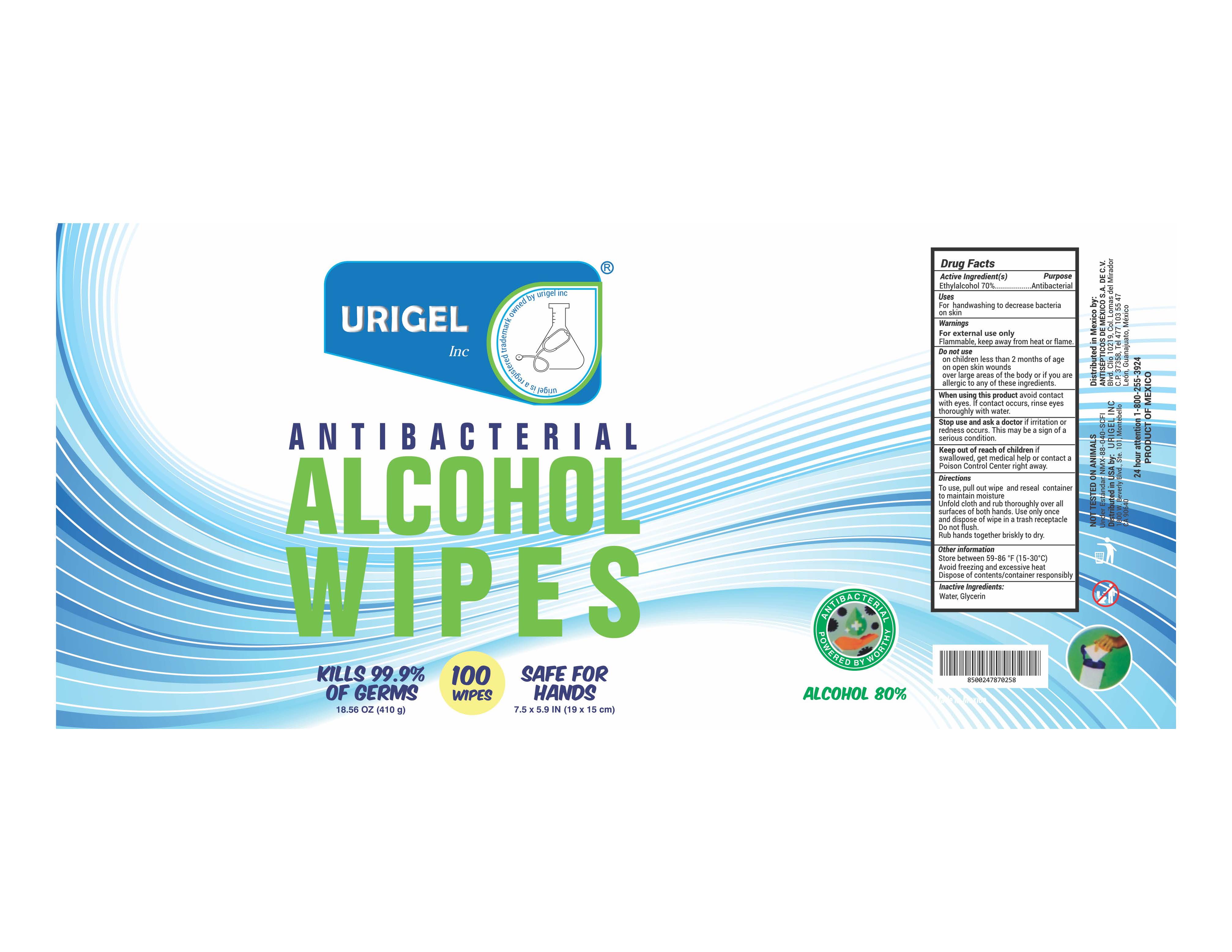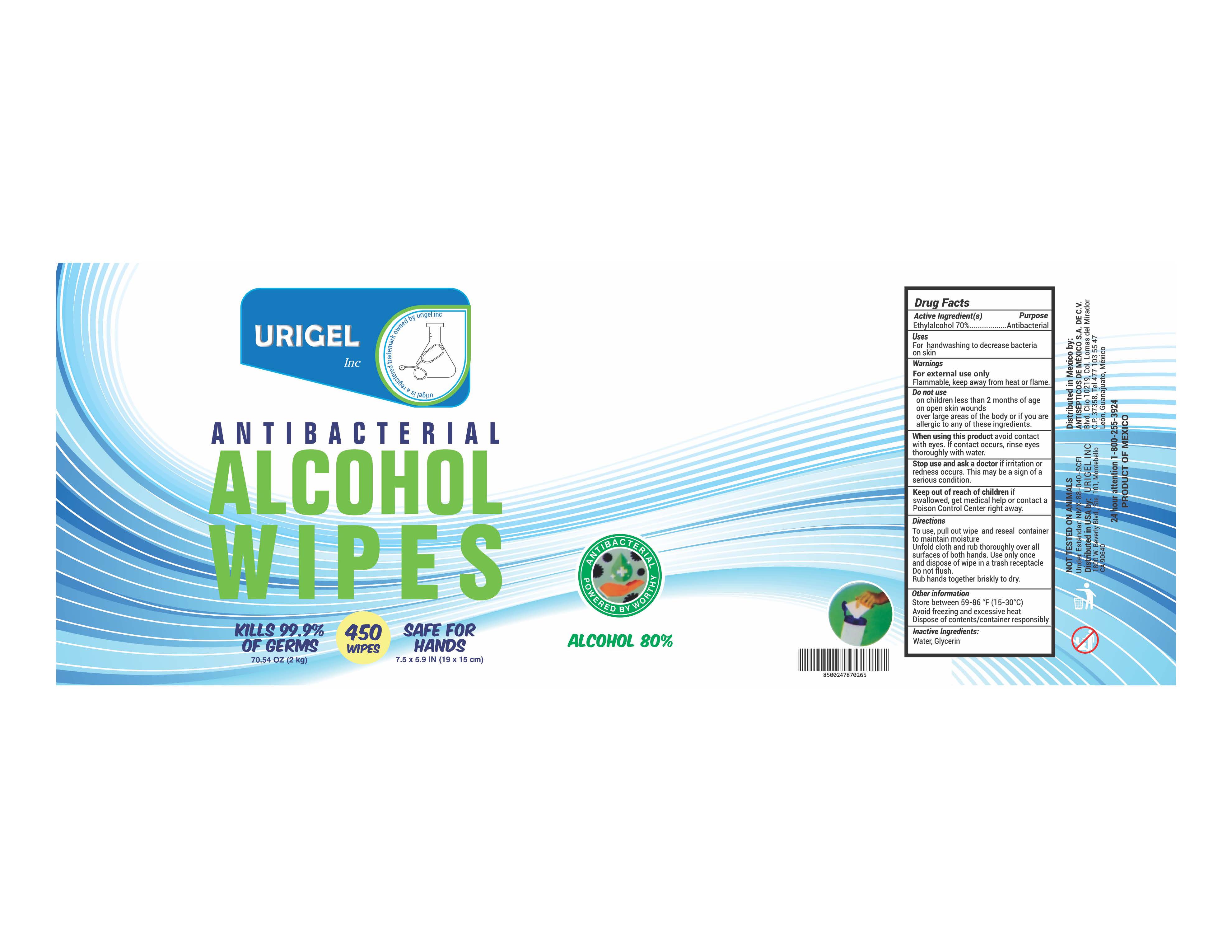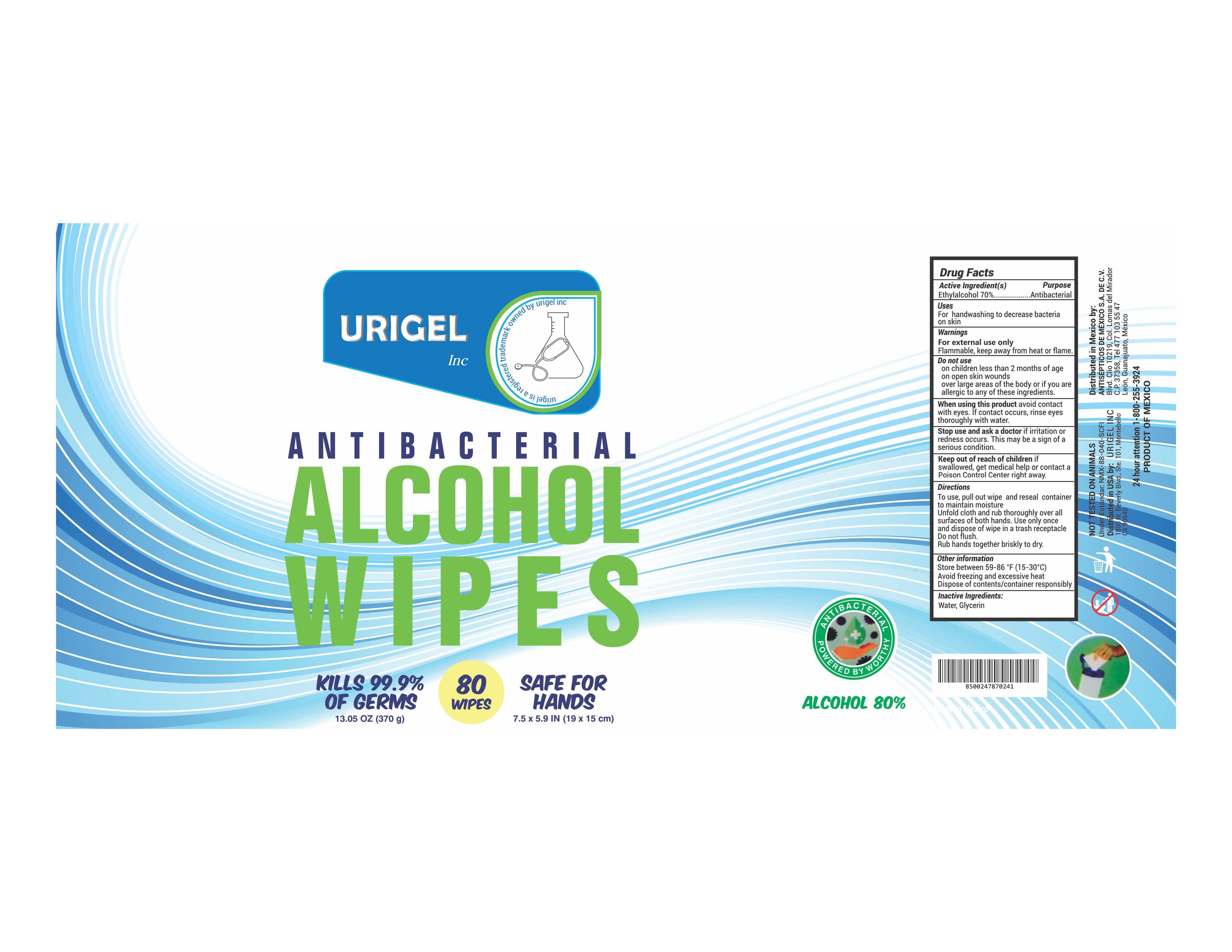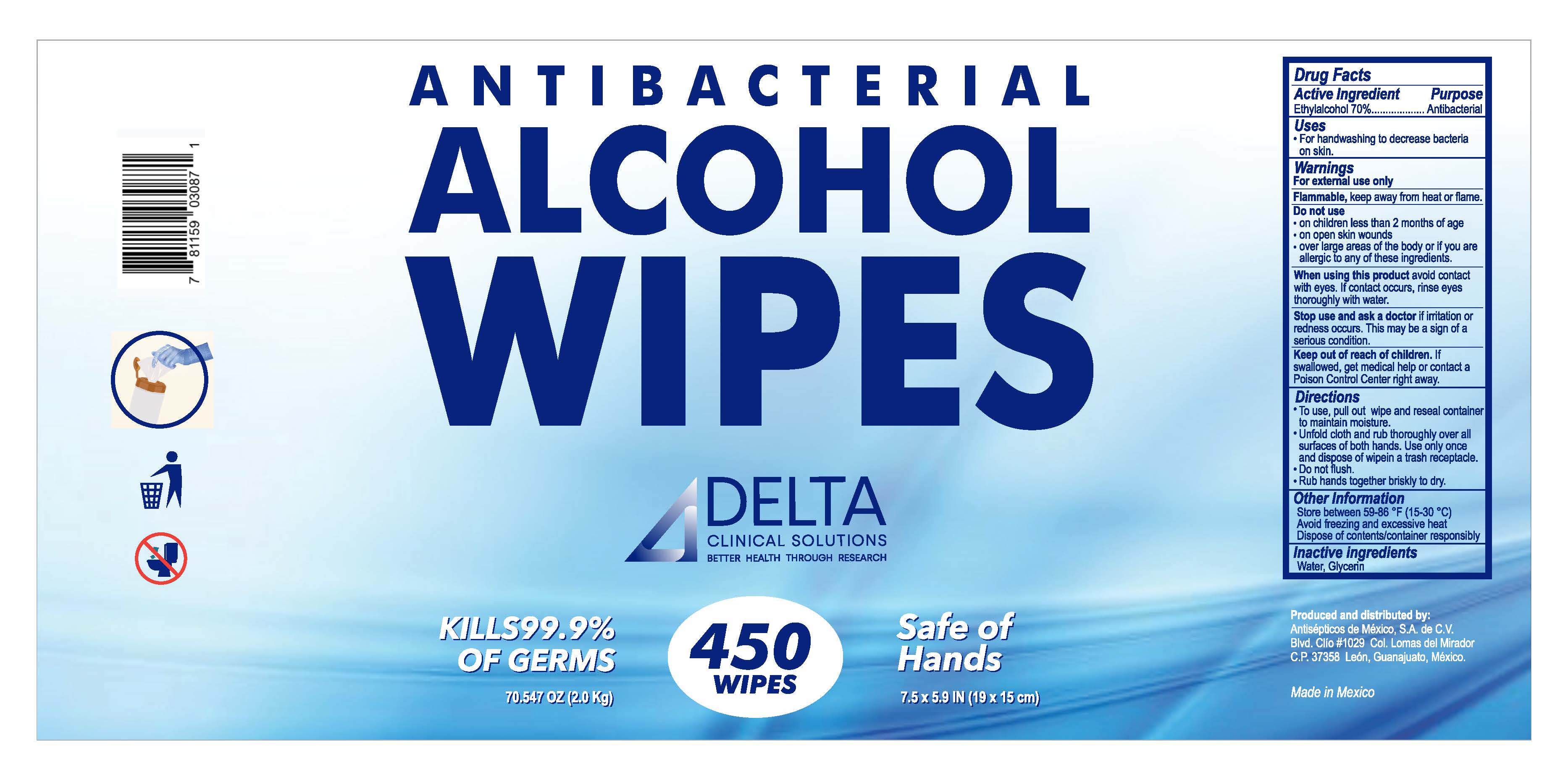 DRUG LABEL: Antibacterial Alcohol Wipes
NDC: 80924-110 | Form: CLOTH
Manufacturer: Urigel
Category: otc | Type: HUMAN OTC DRUG LABEL
Date: 20210106

ACTIVE INGREDIENTS: ALCOHOL 70 g/100 g
INACTIVE INGREDIENTS: GLYCERIN; WATER

Antibacterial Alcohol wipes 80U

Active Ingredient(s)

EthylAlcohol 80%. Purpose: Antibacterial

Purpose

Antibacterial, Hand Sanitizer

Use

For handwashing to decrease bacteria on skin.

Warnings

For external use only. Flammable. Keep away from heat or flame

Do not use

- on children less than 2 months of age
- on open skin wounds
- over large areas of the body or if you are allergic to any of these ingredients.

When using this product avoid contact with eyes. If contact occurs, rinse eyes thoroughly with water.

Stop use and ask a doctor if irritation or rash occurs. These may be signs of a serious condition.

Keep out of reach of children. If swallowed, get medical help or contact a Poison Control Center right away.

Directions

- To use, pull out wipe and reseal container to maintain moisture.
- Unfold cloth and rub thoroughly over all surfaces of both hands. Use only once and dispose of wipein a trash receptacle.
- Do not flush.
- Rub hands together briskly to dry.

Other information

- Store between 59-86 °F (15-30 °C)
- Avoid freezing and excessive heat
- Dispose of contents/container responsibly

Inactive ingredients

Water, Glycerin.

80 each Sanitizer Wipes

80 Each NDC: 80924-110-01

100 Each Sanitizer Wipes

100 Each NDC:80924-110-02

450 Sanitizer Wipes

450 Each NDC:80924-110-03